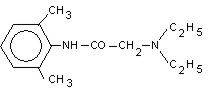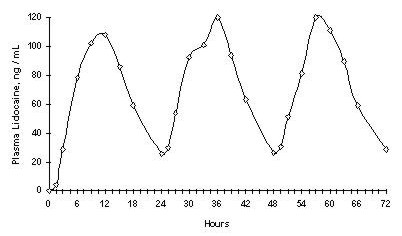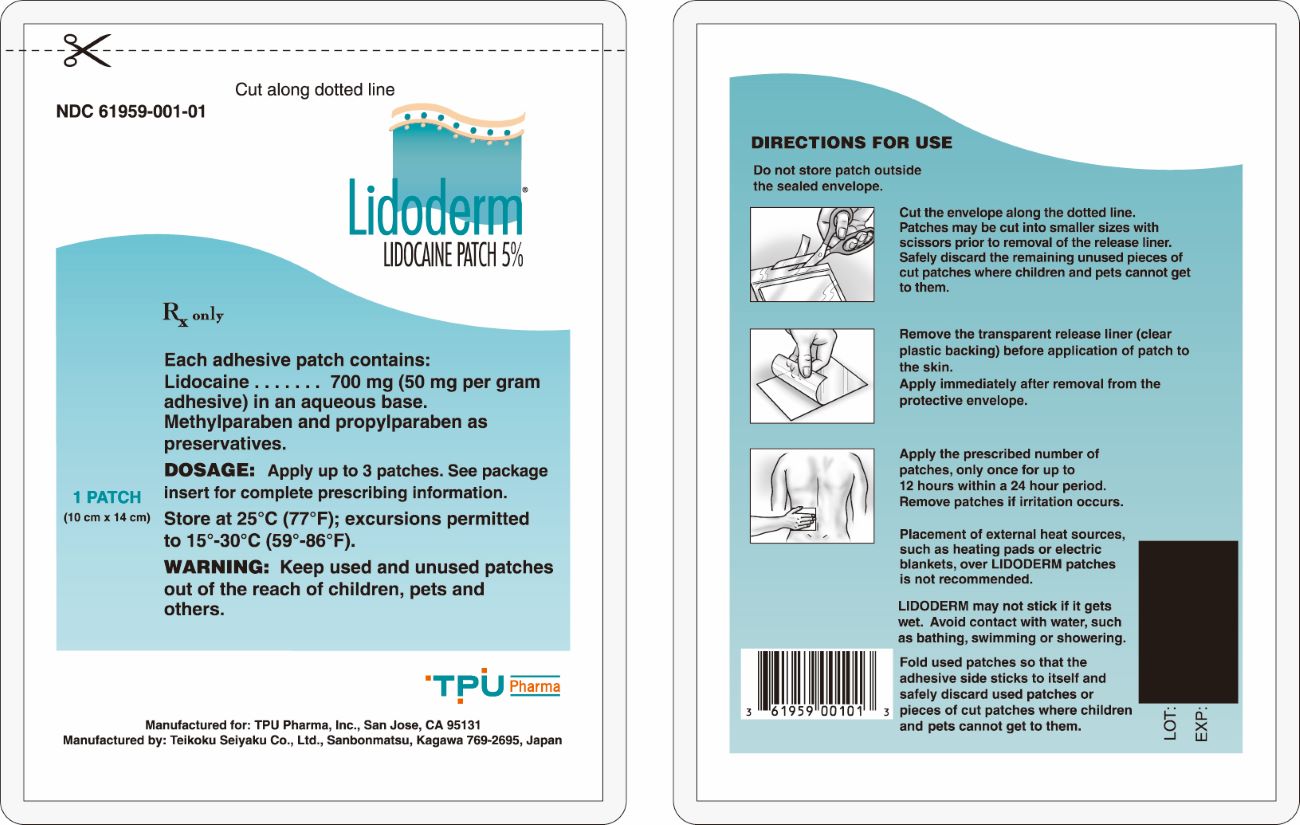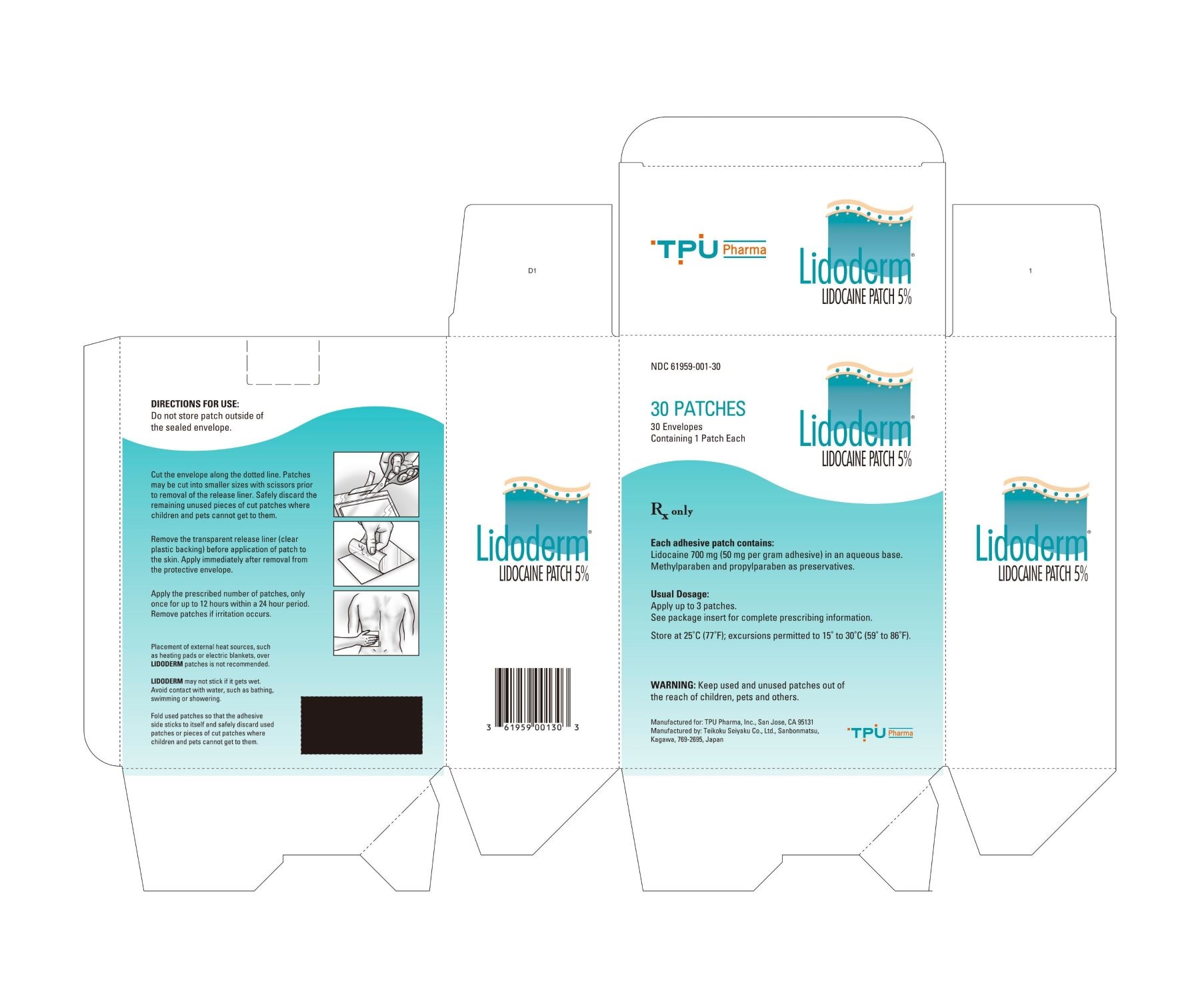 DRUG LABEL: LIDODERM
NDC: 61959-001 | Form: PATCH
Manufacturer: TPU Pharma, Inc.
Category: prescription | Type: HUMAN PRESCRIPTION DRUG LABEL
Date: 20221202

ACTIVE INGREDIENTS: LIDOCAINE 700 mg/1 1

LIDODERM®
(Lidocaine Patch 5%)

Rx only

DESCRIPTION

LIDODERM (lidocaine patch 5%) is comprised of an adhesive material containing 5% lidocaine, which is applied to a non-woven polyester felt backing and covered with a polyethylene terephthalate (PET) film release liner. The release liner is removed prior to application to the skin. The size of the patch is 10 cm × 14 cm.

Lidocaine is chemically designated as acetamide, 2-(diethylamino)-N-(2,6-dimethylphenyl), has an octanol: water partition ratio of 43 at pH 7.4, and has the following structure:

Each adhesive patch contains 700 mg of lidocaine (50 mg per gram adhesive) in an aqueous base. It also contains the following inactive ingredients: dihydroxyaluminum aminoacetate, disodium edetate, gelatin, glycerin, kaolin, methylparaben, polyacrylic acid, polyvinyl alcohol, propylene glycol, propylparaben, sodium carboxymethylcellulose, sodium polyacrylate, D-sorbitol, tartaric acid, and urea.

CLINICAL PHARMACOLOGY

Pharmacodynamics

Lidocaine is an amide-type local anesthetic agent and is suggested to stabilize neuronal membranes by inhibiting the ionic fluxes required for the initiation and conduction of impulses.

The penetration of lidocaine into intact skin after application of LIDODERM is sufficient to produce an analgesic effect, but less than the amount necessary to produce a complete sensory block.

Pharmacokinetics

Absorption
The amount of lidocaine systemically absorbed from LIDODERM is directly related to both the duration of application and the surface area over which it is applied. In a pharmacokinetic study, three LIDODERM patches were applied over an area of 420 cm^2 of intact skin on the back of normal volunteers for 12 hours. Blood samples were withdrawn for determination of lidocaine concentration during the application and for 12 hours after removal of patches. The results are summarized in Table 1.

Table 1
Absorption of lidocaine from LIDODERM
Normal volunteers (n = 15, 12-hour wearing time)
LIDODERM Patch | Application Site | Area (cm^2) | Dose Absorbed (mg) | Cmax mcg/mL) | Tmax (hr)
3 patches (2100 mg) | Back | 420 | 64 ± 32 | 0.13 ± 0.06 | 11 hr

When LIDODERM is used according to the recommended dosing instructions, only 3 ± 2% of the dose applied is expected to be absorbed. At least 95% (665 mg) of lidocaine will remain in a used patch. Mean peak blood concentration of lidocaine is about 0.13 mcg/mL (about 1/10 of the therapeutic concentration required to treat cardiac arrhythmias). Repeated application of three patches simultaneously for 12 hours (recommended maximum daily dose), once per day for three days, indicated that the lidocaine concentration does not increase with daily use. The mean plasma pharmacokinetic profile for the 15 healthy volunteers is shown in Figure 1.

Figure 1
Mean lidocaine blood concentrations after three consecutive daily applications of three LIDODERM patches simultaneously for 12 hours per day in healthy volunteers (n = 15).

Distribution
When lidocaine is administered intravenously to healthy volunteers, the volume of distribution is 0.7 to 2.7 L/kg (mean 1.5 ± 0.6 SD, n = 15). At concentrations produced by application of LIDODERM, lidocaine is approximately 70% bound to plasma proteins, primarily alpha-1-acid glycoprotein. At much higher plasma concentrations (1 to 4 mcg/mL of free base), the plasma protein binding of lidocaine is concentration dependent. Lidocaine crosses the placental and blood brain barriers, presumably by passive diffusion.

Metabolism
It is not known if lidocaine is metabolized in the skin. Lidocaine is metabolized rapidly by the liver to a number of metabolites, including monoethylglycinexylidide (MEGX) and glycinexylidide (GX), both of which have pharmacologic activity similar to, but less potent than that of lidocaine. A minor metabolite, 2,6-xylidine, has unknown pharmacologic activity but is carcinogenic in rats. The blood concentration of this metabolite is negligible following application of LIDODERM (lidocaine patch 5%). Following intravenous administration, MEGX and GX concentrations in serum range from 11 to 36% and from 5 to 11% of lidocaine concentrations, respectively.

Excretion
Lidocaine and its metabolites are excreted by the kidneys. Less than 10% of lidocaine is excreted unchanged. The half-life of lidocaine elimination from the plasma following IV administration is 81 to 149 minutes (mean 107 ± 22 SD, n = 15). The systemic clearance is 0.33 to 0.90 L/min (mean 0.64 ± 0.18 SD, n = 15).

CLINICAL STUDIES

Single-dose treatment with LIDODERM was compared to treatment with vehicle patch (without lidocaine), and to no treatment (observation only) in a double-blind, crossover clinical trial with 35 post-herpetic neuralgia patients. Pain intensity and pain relief scores were evaluated periodically for 12 hours. LIDODERM performed statistically better than vehicle patch in terms of pain intensity from 4 to 12 hours.

Multiple-dose, two-week treatment with LIDODERM was compared to vehicle patch (without lidocaine) in a double-blind, crossover clinical trial of withdrawal-type design conducted in 32 patients, who were considered as responders to the open-label use of LIDODERM prior to the study. The constant type of pain was evaluated but not the pain induced by sensory stimuli (dysesthesia). Statistically significant differences favoring LIDODERM were observed in terms of time to exit from the trial (14 versus 3.8 days at p-value <0.001), daily average pain relief, and patient's preference of treatment. About half of the patients also took oral medication commonly used in the treatment of post-herpetic neuralgia. The extent of use of concomitant medication was similar in the two treatment groups.

INDICATION AND USAGE

LIDODERM is indicated for relief of pain associated with post-herpetic neuralgia. It should be applied only to intact skin.

CONTRAINDICATIONS

LIDODERM is contraindicated in patients with a known history of sensitivity to local anesthetics of the amide type, or to any other component of the product.

WARNINGS

Risk of Methemoglobinemia

Cases of methemoglobinemia have been reported in association with local anesthetic use. Although all patients are at risk for methemoglobinemia, patients with glucose-6-phosphate dehydrogenase deficiency, congenital or idiopathic methemoglobinemia, cardiac or pulmonary compromise, infants under 6 months of age, and concurrent exposure to oxidizing agents or their metabolites are more susceptible to developing clinical manifestations of the condition. If local anesthetics must be used in these patients, close monitoring for symptoms and signs of methemoglobinemia is recommended.

Signs of methemoglobinemia may occur immediately or may be delayed some hours after exposure, and are characterized by a cyanotic skin discoloration and/or abnormal coloration of the blood. Methemoglobin levels may continue to rise; therefore, immediate treatment is required to avert more serious central nervous system and cardiovascular adverse effects, including seizures, coma, arrhythmias, and death. Discontinue LIDODERM and any other oxidizing agents. Depending on the severity of the signs and symptoms, patients may respond to supportive care, i.e., oxygen therapy, hydration. A more severe clinical presentation may require treatment with methylene blue, exchange transfusion, or hyperbaric oxygen.

Accidental Exposure in Children

Even a used LIDODERM patch contains a large amount of lidocaine (at least 665 mg). The potential exists for a small child or a pet to suffer serious adverse effects from chewing or ingesting a new or used LIDODERM patch, although the risk with this formulation has not been evaluated. It is important for patients to store and dispose of LIDODERM out of the reach of children, pets and others. (See HANDLING AND DISPOSAL)

Excessive Dosing

Excessive dosing by applying LIDODERM to larger areas or for longer than the recommended wearing time could result in increased absorption of lidocaine and high blood concentrations, leading to serious adverse effects (see ADVERSE REACTIONS, Systemic Reactions). Lidocaine toxicity could be expected at lidocaine blood concentrations above 5 mcg/mL. The blood concentration of lidocaine is determined by the rate of systemic absorption and elimination. Longer duration of application, application of more than the recommended number of patches, smaller patients, or impaired elimination may all contribute to increasing the blood concentration of lidocaine. With recommended dosing of LIDODERM, the average peak blood concentration is about 0.13 mcg/mL, but concentrations higher than 0.25 mcg/mL have been observed in some individuals.

PRECAUTIONS

General

Hepatic Disease
Patients with severe hepatic disease are at greater risk of developing toxic blood concentrations of lidocaine, because of their inability to metabolize lidocaine normally.

Allergic Reactions
Patients allergic to para-aminobenzoic acid derivatives (procaine, tetracaine, benzocaine, etc.) have not shown cross sensitivity to lidocaine. However, LIDODERM should be used with caution in patients with a history of drug sensitivities, especially if the etiologic agent is uncertain.

Non-intact Skin
Application to broken or inflamed skin, although not tested, may result in higher blood concentrations of lidocaine from increased absorption. LIDODERM is only recommended for use on intact skin.

External Heat Sources
Placement of external heat sources, such as heating pads or electric blankets, over LIDODERM patches is not recommended as this has not been evaluated and may increase plasma lidocaine levels.

Eye Exposure
The contact of LIDODERM with eyes, although not studied, should be avoided based on the findings of severe eye irritation with the use of similar products in animals. If eye contact occurs, immediately wash out the eye with water or saline and protect the eye until sensation returns.

Information for Patients

Methemoglobinemia

Inform patients that use of local anesthetics may cause methemoglobinemia, a serious condition that must be treated promptly. Advise patients or caregivers to stop use and seek immediate medical attention if they or someone in their care experience the following signs or symptoms: pale, gray, or blue colored skin (cyanosis); headache; rapid heart rate; shortness of breath; lightheadedness; or fatigue.

Drug Interactions

Antiarrhythmic Drugs
LIDODERM should be used with caution in patients receiving Class I antiarrhythmic drugs (such as tocainide and mexiletine) since the toxic effects are additive and potentially synergistic.

Local Anesthetics
When LIDODERM is used concomitantly with other products containing local anesthetic agents, the amount absorbed from all formulations must be considered.

Drugs That May Cause Methemoglobinemia When Used with LIDODERM

Patients who are administered local anesthetics are at increased risk of developing methemoglobinemia when concurrently exposed to the following drugs, which could include other local anesthetics:

Examples of Drugs Associated with Methemoglobinemia:

Class | Examples
Nitrates/Nitrites | nitric oxide, nitroglycerin, nitroprusside, nitrous oxide
Local anesthetics | articaine, benzocaine, bupivacaine, lidocaine, mepivacaine, prilocaine, procaine, ropivacaine, tetracaine
Antineoplastic agents | cyclophosphamide, flutamide, hydroxyurea, ifosfamide, rasburicase
Antibiotics | dapsone, nitrofurantoin, para-aminosalicylic acid, sulfonamides
Antimalarials | chloroquine, primaquine
Anticonvulsants | Phenobarbital, phenytoin, sodium valproate
Other drugs | acetaminophen, metoclopramide, quinine, sulfasalazine

Carcinogenesis, Mutagenesis, Impairment of Fertility

Carcinogenesis
A minor metabolite, 2,6-xylidine, has been found to be carcinogenic in rats. The blood concentration of this metabolite is negligible following application of LIDODERM.

Mutagenesis
Lidocaine HCl is not mutagenic in Salmonella/mammalian microsome test nor clastogenic in chromosome aberration assay with human lymphocytes and mouse micronucleus test.

Impairment of Fertility
The effect of LIDODERM on fertility has not been studied.

Pregnancy

Teratogenic Effects
Pregnancy Category B.
LIDODERM (lidocaine patch 5%) has not been studied in pregnancy. Reproduction studies with lidocaine have been performed in rats at doses up to 30 mg/kg subcutaneously and have revealed no evidence of harm to the fetus due to lidocaine. There are, however, no adequate and well-controlled studies in pregnant women. Because animal reproduction studies are not always predictive of human response, LIDODERM should be used during pregnancy only if clearly needed.

Labor and Delivery

LIDODERM has not been studied in labor and delivery. Lidocaine is not contraindicated in labor and delivery. Should LIDODERM be used concomitantly with other products containing lidocaine, total doses contributed by all formulations must be considered.

Nursing Mothers

LIDODERM has not been studied in nursing mothers. Lidocaine is excreted in human milk, and the milk:plasma ratio of lidocaine is 0.4. Caution should be exercised when LIDODERM is administered to a nursing woman.

Pediatric Use

Safety and effectiveness in pediatric patients have not been established.

ADVERSE REACTIONS

Application Site Reactions

During or immediately after treatment with LIDODERM (lidocaine patch 5%), the skin at the site of application may develop blisters, bruising, burning sensation, depigmentation, dermatitis, discoloration, edema, erythema, exfoliation, irritation, papules, petechia, pruritus, vesicles, or may be the locus of abnormal sensation. These reactions are generally mild and transient, resolving spontaneously within a few minutes to hours.

Allergic Reactions

Allergic and anaphylactoid reactions associated with lidocaine, although rare, can occur. They are characterized by angioedema, bronchospasm, dermatitis, dyspnea, hypersensitivity, laryngospasm, pruritus, shock, and urticaria. If they occur, they should be managed by conventional means. The detection of sensitivity by skin testing is of doubtful value.

Other Adverse Events

Due to the nature and limitation of spontaneous reports in postmarketing surveillance, causality has not been established for additional reported adverse events including:

Asthenia, confusion, disorientation, dizziness, headache, hyperesthesia, hypoesthesia, lightheadedness, metallic taste, nausea, nervousness, pain exacerbated, paresthesia, somnolence, taste alteration, vomiting, visual disturbances such as blurred vision, flushing, tinnitus, and tremor.

Systemic (Dose-Related) Reactions

Systemic adverse reactions following appropriate use of LIDODERM are unlikely, due to the small dose absorbed (see CLINICAL PHARMACOLOGY, Pharmacokinetics). Systemic adverse effects of lidocaine are similar in nature to those observed with other amide local anesthetic agents, including CNS excitation and/or depression (light headedness, nervousness, apprehension, euphoria, confusion, dizziness, drowsiness, tinnitus, blurred or double vision, vomiting, sensations of heat, cold or numbness, twitching, tremors, convulsions, unconsciousness, respiratory depression and arrest). Excitatory CNS reactions may be brief or not occur at all, in which case the first manifestation may be drowsiness merging into unconsciousness. Cardiovascular manifestations may include bradycardia, hypotension and cardiovascular collapse leading to arrest.

OVERDOSAGE

Lidocaine overdose from cutaneous absorption is rare, but could occur. If there is any suspicion of lidocaine overdose (see ADVERSE REACTIONS, Systemic Reactions), drug blood concentration should be checked. The management of overdose includes close monitoring, supportive care, and symptomatic treatment. Dialysis is of negligible value in the treatment of acute overdose with lidocaine.

In the absence of massive topical overdose or oral ingestion, evaluation of symptoms of toxicity should include consideration of other etiologies for the clinical effects, or overdosage from other sources of lidocaine or other local anesthetics.

The oral LD50 of lidocaine HCl is 459 (346-773) mg/kg (as the salt) in non-fasted female rats and 214 (159-324) mg/kg (as the salt) in fasted female rats, which are equivalent to roughly 4000 mg and 2000 mg, respectively, in a 60 to 70 kg man based on the equivalent surface area dosage conversion factors between species.

DOSAGE AND ADMINISTRATION

Apply LIDODERM to intact skin to cover the most painful area. Apply the prescribed number of patches (maximum of 3), only once for up to 12 hours within a 24 hour period. Patches may be cut into smaller sizes with scissors prior to removal of the release liner. (See HANDLING AND DISPOSAL) Clothing may be worn over the area of application. Smaller areas of treatment are recommended in a debilitated patient, or a patient with impaired elimination.

If irritation or a burning sensation occurs during application, remove the patch(es) and do not reapply until the irritation subsides.

When LIDODERM is used concomitantly with other products containing local anesthetic agents, the amount absorbed from all formulations must be considered.

LIDODERM may not stick if it gets wet. Avoid contact with water, such as bathing, swimming or showering.

HANDLING AND DISPOSAL

Hands should be washed after the handling of LIDODERM, and eye contact with LIDODERM should be avoided. Do not store patch outside the sealed envelope. Apply immediately after removal from the protective envelope. Fold used patches so that the adhesive side sticks to itself and safely discard used patches or pieces of cut patches where children and pets cannot get to them. LIDODERM should be kept out of the reach of children.

HOW SUPPLIED

LIDODERM (lidocaine patch 5%) is available as the following:

Carton of 30 patches, packaged into individual child-resistant envelopes
NDC 61959-001-30

Store at 25°C (77°F); excursions permitted to 15°-30°C (59°-86°F). [See USP Controlled Room Temperature].

For more information, call Endo Pharmaceuticals at 1-800-405-1388.

Manufactured for:
TPU Pharma, Inc.
San Jose, CA 95131

Revised: December 2022

PACKAGE LABEL

Package Label - Principal Display Panel – 1 Count Pouch, Lidoderm Patch

PACKAGE LABEL

Package Label - Principal Display Panel – 30 Count Carton, Lidoderm Patch